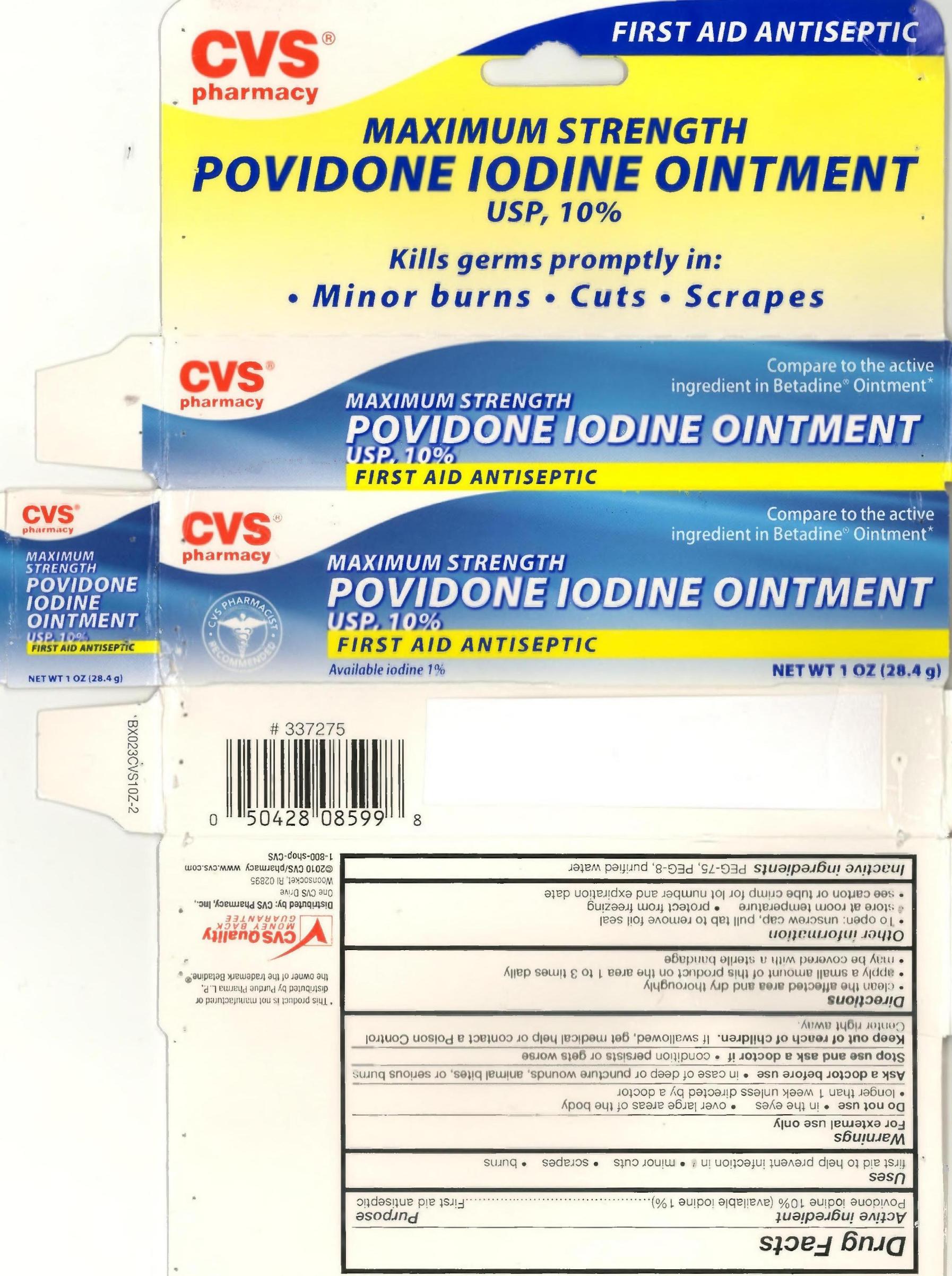 DRUG LABEL: POVIDONE IODINE
NDC: 59779-085 | Form: OINTMENT
Manufacturer: CVS Pharmacy
Category: otc | Type: HUMAN OTC DRUG LABEL
Date: 20110204

ACTIVE INGREDIENTS: POVIDONE-IODINE 1 g/10 g
INACTIVE INGREDIENTS: POLYETHYLENE GLYCOL 4000 2.5 g/10 g; WATER 0.5 g/10 g; POLYETHYLENE GLYCOL 400 6 g/10 g

drug facts

ACTIVE INGREDIENT

Section from Tube Label Follows:
Active Ingredient Purpose
Povidone iodine 10%
(available iodine 1%) ............................First aid antiseptic
Section from Carton Label Follows:
Active ingredient Purpose
Povidone iodine 1% (available iodine 1%)........................................First aid antiseptic

PURPOSE

Section from Tube Label Follows:
Active Ingredient Purpose
Povidone iodine 10%
(available iodine 1%) ............................First aid antiseptic
Uses first aid to help prevent infection in
- minor cuts - scrapes - burns
Section from Carton Label Follows:
Active ingredient Purpose
Povidone iodine 1% (available iodine 1%)........................................First aid antiseptic
Uses
first aid to help prevent infection in - minor cuts - scrapes - burns

KEEP OUT OF REACH OF CHILDREN

Section from Warnings portion of tube label follows:
Keep out of reach of children. If swallowed, get medical help or
contact a Poison Control Center right away.
Section from Warnings section of Carton label follows:
Keep out of reach of children. If swallowed, get medical help or contact a Poison
Control Center right away.

INDICATIONS AND USAGE

Section from Directions portion of tube label follows:
Directions - clean the affected area and dry thoroughly
- apply a small amount of this product on the area 1 to 3 times
daily - May be covered with a sterile bandage
Section from Directions portion of carton label follows:
Directions
- clean the affected area and dry thoroughly
- apply a small amount of this product on the area 1 to 3 times daily
- May be covered with a sterile bandage

From Warnings Section of Tube Label:
Warnings For external use only. Do not use - In the eyes
- over large areas of the body - longer than 1 week unless
directed by a doctor. Ask a doctor before use - in case of deep
or puncture wounds, animal bites, or serious burns. Stop use
and ask a doctor if - condition persists or gets worse. Keep
out of reach of children. If swallowed, get medical help or
contact a Poison Control Center right away.
From Warnings Section of Carton Label:
Warnings
For external use only.
Do not use - In the eyes - over large areas of the body
- longer than 1 week unless directed by a doctor.
Ask a doctor before use - in case of deep or puncture wounds, animal bites, or serious burns.
Stop use and ask a doctor if - condition persists or gets worse.
Keep out of reach of children. If swallowed, get medical help or contact a Poison Control
Center right away.

DOSAGE AND ADMINISTRATION

Section from Directions portion of tube label follows:
Directions - clean the affected area and dry thoroughly
- apply a small amount of this product on the area 1 to 3 times
daily - May be covered with a sterile bandage
Section from Directions portion of carton label follows:
Directions
- clean the affected area and dry thoroughly
- apply a small amount of this product on the area 1 to 3 times daily
- May be covered with a sterile bandage

From Inactive Ingredients section of Tube Label:
Inactive Ingredients PEG-75, PEG-8, purified water
From Inactive Ingredients section of Carton Label:
Inactive Ingredients PEG-75, PEG-8, purified water

PACKAGE LABEL

Carton